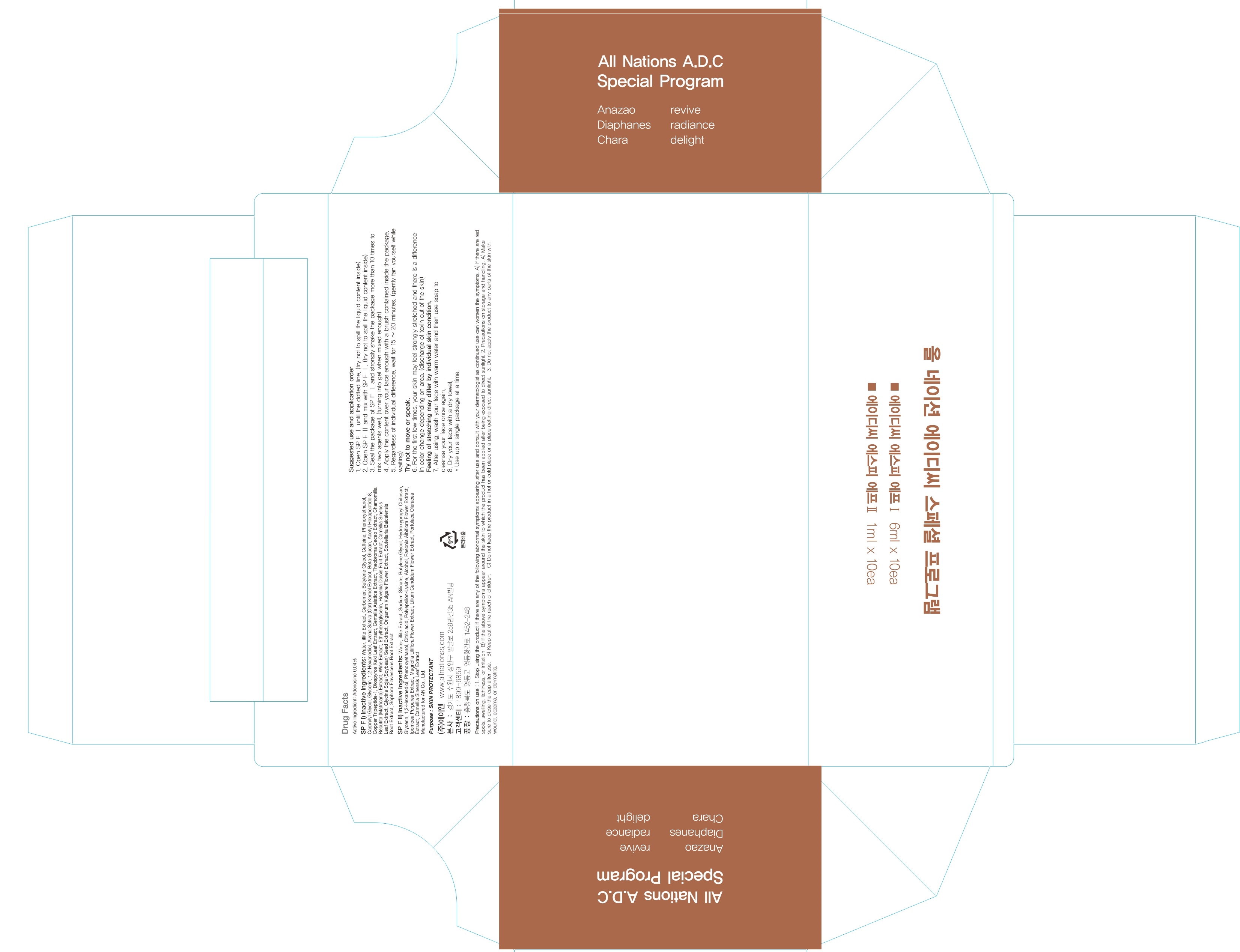 DRUG LABEL: All Nations A D C Special Program
NDC: 69153-130 | Form: SOLUTION
Manufacturer: AN Co Ltd.
Category: otc | Type: HUMAN OTC DRUG LABEL
Date: 20170627

ACTIVE INGREDIENTS: Adenosine 0.002 g/6 mL
INACTIVE INGREDIENTS: Water; Butylene Glycol

ACTIVE INGREDIENT

Active ingredients: Adenosine 0.04%

INACTIVE INGREDIENT

Inactive ingredients:

SP F I) Water, illite Extract, Carbomer, Butylene Glycol, Caffeine, Phenoxyethanol, Carprylyl Glycol, Glycerin, 1,2-Hexanediol, Avena Sativa (Oat) Kernel Extract, Beta-Glucan, Acetyl Hexapeptide-8, Copper Tripeptide-1, Diospyros Kaki Leaf Extract, Centella Asiatica Extract, Theobroma Cacao Extract, Chamomilla Recutita (Matricaria) Extract, Wine Extract, Ethylhexylglycerin, Hovenia Dulcis Fruit Extract, Camellia Sinensis Leaf Extract, Glycine Soja (Soybean) Seed Extract, Origanum Vulgare Flower Extract, Scutellaria Baicalensis Root Extract, Sophora Flavescens Root Extract

SP F II) Water, illite Extract, Sodium Silicate, Butylene Glycol, Hydroxypropyl Chitosan, Glycerin, 1,2-Hexanediol, Phenoxyethanol, Citric acid, Polyepsilon-Lysine, Alcohol, Paeonia Albiflora Flower Extract, Ipomoea Purpurea Extract, Magnolia Liliflora Flower Extract, Lilium Candidum Flower Extract, Portulaca Oleracea Extract, Camellia Sinensis Leaf Extract

Volume) SP F I: 6mL, SP F II: 1mL

PURPOSE

Purpose: SKIN PROTECTANT

Precautions on use: 1. Stop using the product if there are any of the following abnormal symptoms appearing after use and consult with your dermatologist as continued use can worsen the symptoms. A) If there are red spots, swelling, itchiness, or irritation B) If the above symptoms appear around the skin to which the product has been applied after being exposed to direct sunlight. 2. Precautions on storage and handling. A) Make sure to close the cap after use. B) Keep out of the reach of children. C) Do not keep the product in a hot or cold place or a place getting direct sunlight. 3. Do not apply the product to any parts of the skin with wound, eczema, or dermatitis.

KEEP OUT OF REACH OF CHILDREN

INDICATIONS & USAGE

Suggested use and application order:

1. Open SP F Ⅰ until the dotted line. (try not to spill the liquid content inside) 2. Open SP F Ⅱ and mix with SP F Ⅰ. (try not to spill the liquid content inside) 3. Seal the package of SP F Ⅰ and strongly shake the package more than 10 times to mix two agents well. (turning into gel when mixed enough) 4. Apply the content over your face enough with a brush contained inside the package. 5. Regardless of individual difference, wait for 15 ~ 20 minutes. (gently fan yourself while waiting) Try not to move or speak. 6. For the first few times, your skin may feel strongly stretched and there is a difference in color change depending on area. (discharge of toxin out of the skin) Feeling of stretching may differ by individual skin condition. 7. After using wash your face with warm water and then use soap to cleanse your face once again. 8. Dry your face with a dry towel.

*Use up a single package at a time.

DOSAGE & ADMINISTRATION

Suggested use and application order:

1. Open SP F Ⅰ until the dotted line. (try not to spill the liquid content inside) 2. Open SP F Ⅱ and mix with SP F Ⅰ. (try not to spill the liquid content inside) 3. Seal the package of SP F Ⅰ and strongly shake the package more than 10 times to mix two agents well. (turning into gel when mixed enough) 4. Apply the content over your face enough with a brush contained inside the package. 5. Regardless of individual difference, wait for 15 ~ 20 minutes. (gently fan yourself while waiting) Try not to move or speak. 6. For the first few times, your skin may feel strongly stretched and there is a difference in color change depending on area. (discharge of toxin out of the skin) Feeling of stretching may differ by individual skin condition. 7. After using wash your face with warm water and then use soap to cleanse your face once again. 8. Dry your face with a dry towel.

*Use up a single package at a time.